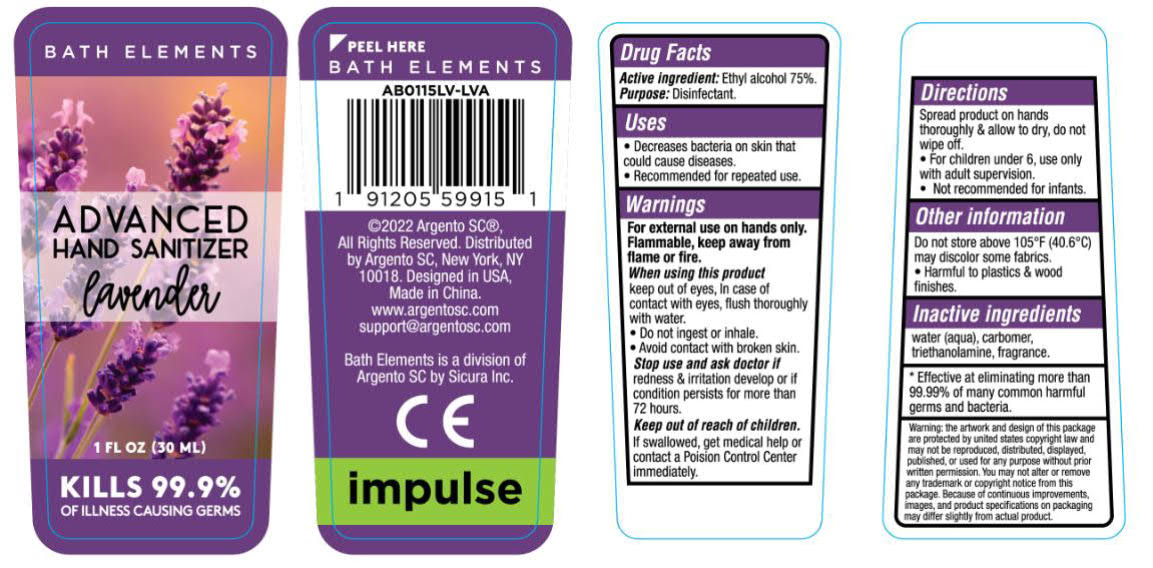 DRUG LABEL: BATH ELEMENTS ADVANCED HAND SANITIZER LAVENDER
NDC: 82534-203 | Form: GEL
Manufacturer: Hangzhou Beite Daily Necessities Co., Ltd.
Category: otc | Type: HUMAN OTC DRUG LABEL
Date: 20220707

ACTIVE INGREDIENTS: ALCOHOL 22.5 mL/30 mL
INACTIVE INGREDIENTS: FRAGRANCE LAVENDER ORC1800979; WATER; TROLAMINE; CARBOMER 940

75% Alcohol Sanitizer - Lavender

Active Ingredient(s)

Ethyl Alcohol, 75% v/v. Purpose: Disinfectant

Purpose

Disinfectant

Uses

- Decreases bacteria on skin that could cause diseases.
- Recommended for repeated use.

Warnings

For external use on hands only.

Flammable, keep away from flame or fire.

When using this product

keep out of eyes, in case of contact with eyes, flush thoroughly with water.

- Do not ingest or inhale.
- Avoid contact with broken skin.

Stop use and ask doctor if

redness & irritation develop or if condition persists for more than 72 hours.

Keep out of reach of children.

If swallowed, get medical help or contact a Poision Control Center immediately.

DO NOT USE

- For children under 6, use only with adult supervision.
- Not recommended for infants.

When using this product

keep out of eyes, in case of contact with eyes, flush thoroughly with water.

- Do not ingest or inhale.
- Avoid contact with broken skin.

Stop use and ask doctor if

redness & irritation develop or if condition persists for more than 72 hours

Keep out of reach of children.

If swallowed, get medical help or contact a Poision Control Center immediately.

Directions

Spread product on hands thoroughly & allow to dry, do not wipe off.

- For children under 6, use only with adult supervision.
- Not recommended for infants.

Other information

Do not store above 105℉ (40.6℃).

may discolor some fabrics.

- Harmful to plastics & wood finishes.

Inactive ingredients

water (aqua), carbomer, triethanolamine, fragrance.